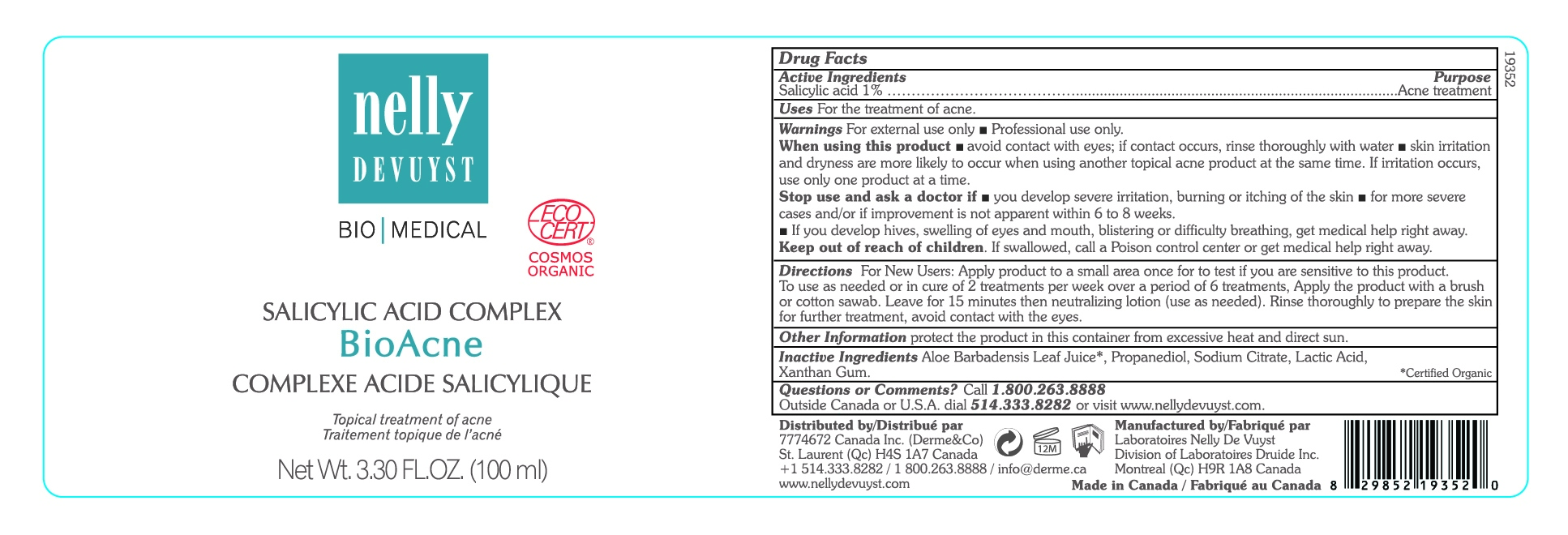 DRUG LABEL: NELLY DEVUYST SALICYLIC ACID COMPLEX BIOACNE
NDC: 71447-010 | Form: LIQUID
Manufacturer: LABORATOIRES DRUIDE INC
Category: otc | Type: HUMAN OTC DRUG LABEL
Date: 20210101

ACTIVE INGREDIENTS: SALICYLIC ACID 1 g/100 mL
INACTIVE INGREDIENTS: ALOE VERA LEAF; PROPANEDIOL; SODIUM CITRATE; LACTIC ACID; XANTHAN GUM

NELLY DEVUYST SALICYLIC ACID COMPLEX BIOACNE 100 mL

Active Ingredients

Salicylic Acid 1%

Purpose

Acne Treatment

Uses

Penetrates pores to control or reduce acne pimples.

Warnings

▪ For external use only ▪ Professional use only.

When using this product

▪ avoid contact with eyes. If contact occurs, rinse thoroughly with water ▪ Skin irritation and dryness are more likely to occur when using another topical acne product at the same time. If irritation occurs, use only one product at a time.

and ask a doctor if

▪ you develop severe irritation, burning or itching of the skin ▪ for more severe cases and or if improvement is not apparent within 6 to 8 weeks ▪ If you develop hives, swelling of eyes and mouth, blistering or difficulty breathing, get medical help right away.

Keep out of reach of children

If swallowed, get medical help or contact a Poison Control Center right away.

Directions

▪ New users: apply product to a small area once a day to test if you are sensitive to this product.

▪ Apply product with a brush or cotton swab.

▪ Leave for 15 minutes, then use a neutralizing lotion.

▪ Rinse thoroughly to prepare the skin for further treatment.

▪ Use for up to 6 treatments.

Other Information

Protect the product in this container from excessive heat and direct sun.

Inactive Ingredients

Aloe Barbadensis Leaf Juice*, Propanediol, Sodium Citrate, Lactic Acid, Xanthan Gum.

Certified organic*

Questions or Comments?

Call +1 800-263-8888

Outside Canada or United States, dial +1 514-333-8282, or visit www.nellydevuyst.com

Distributed by

7774672 Canada Inc (Derme & Co)

4980 Chemin Bois Franc

St. Laurent, QC H4S 1A7

Canada

T: +1 514-333-8282, T: +1 800-263-8888

www.nellydevuyst.com

Made in Canada